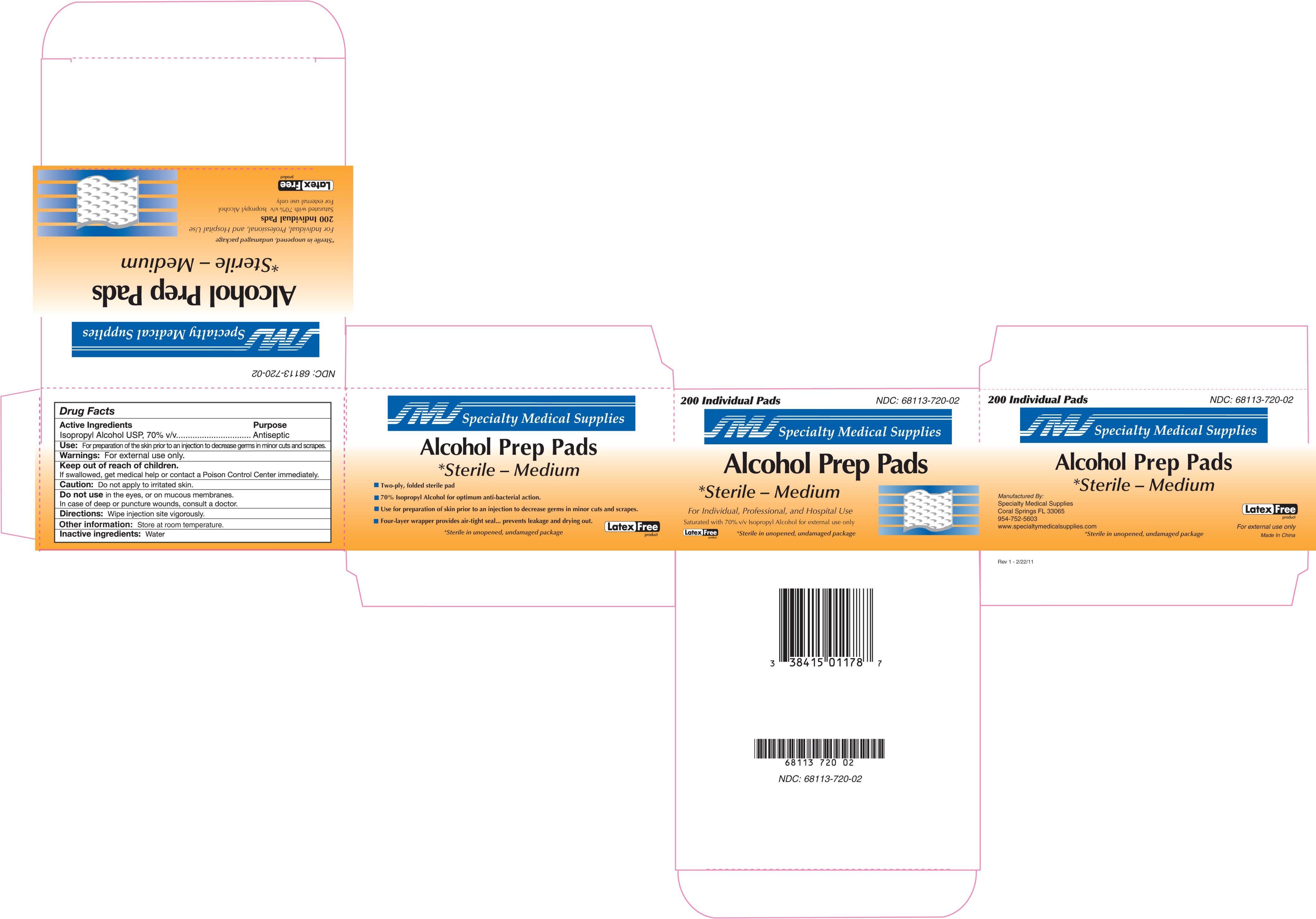 DRUG LABEL: Sterile Alcohol Prep Pad
NDC: 68113-720 | Form: LIQUID
Manufacturer: Caribbean Medical Brokers
Category: otc | Type: HUMAN OTC DRUG LABEL
Date: 20110304

ACTIVE INGREDIENTS: Alcohol 0.8 g/1 mL
INACTIVE INGREDIENTS: Water

Alcohol Prep Pad Sterile - Medium

Active Ingredients:

Isopropyl Alcohol USP, 70% v/v

Purpose

Antiseptic

INDICATIONS AND USAGE

Use: For preparation of skin prior to an injection to decrease germs in minor cuts and scrapes.

Warnings: For external use only.

Keep out of reach of children. If swallowed, get medical help or contact a Poison Control Center right away.

GENERAL PRECAUTIONS

Caution: Do not apply to irritated skin.

Do not use in the eyes or on mucous membranes. In case of deep or puncture wounds, consult a doctor.

DOSAGE AND ADMINISTRATION

Directions: Wipe injection site vigorously.

Other information: Store at room temperature.

Inactive Ingredients: Water

Manufactured by:

Specialty Medical Supplies

Coral Springs, FL 33065

954-752-5603

www.specialtymedicalsupplies.com

Made in China

PACKAGE LABEL

200 Individual Pads

NDC: 68113-720-02

Specialty Medical Supplies

Alcohol Prep Pads

*Sterile - Medium

Antiseptic for preparation of the skin prior to injection

For Individual, Professional, and Hospital Use

Saturated with 70% v/v Isopropyl Alcohol for external use only

*Sterile in unopened, undamaged package.

Sterile Prep Pad Labeling.jpg
Sterile Prep Pad Labeling.jpg